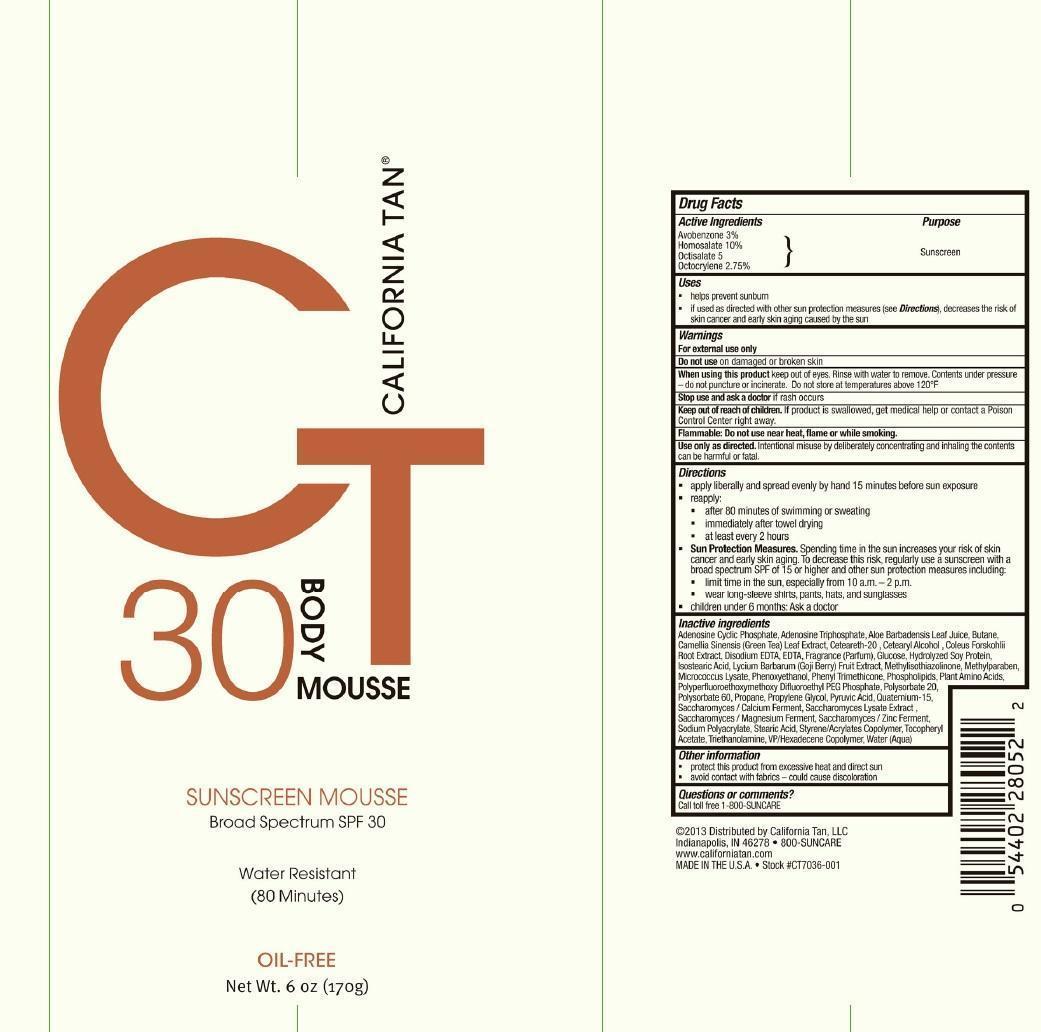 DRUG LABEL: California Tan
NDC: 13630-0079 | Form: AEROSOL, FOAM
Manufacturer: Prime Packaging, Inc.
Category: otc | Type: HUMAN OTC DRUG LABEL
Date: 20181219

ACTIVE INGREDIENTS: AVOBENZONE 300 g/1 g; HOMOSALATE 1000 g/1 g; OCTISALATE 500 g/1 g; OCTOCRYLENE 275 g/1 g
INACTIVE INGREDIENTS: ALOE VERA LEAF; BUTANE; PROPANE; CETYL ALCOHOL; SODIUM POLYACRYLATE (8000 MW); POLYSORBATE 60; EDETATE DISODIUM; ISOSTEARIC ACID; METHYLISOTHIAZOLINONE; PHENOXYETHANOL; PHENYL TRIMETHICONE; POLYSORBATE 20; PROPYLENE GLYCOL; GREEN TEA LEAF; LYCIUM BARBARUM FRUIT; STEARIC ACID; CETEARETH-22; STYRENE/ACRYLAMIDE COPOLYMER (MW 500000); .ALPHA.-TOCOPHEROL ACETATE; TROLAMINE; VINYLPYRROLIDONE/HEXADECENE COPOLYMER; EGG PHOSPHOLIPIDS; AMINO ACIDS; SACCHAROMYCES LYSATE; SOY PROTEIN; CALCIUM; MAGNESIUM; ZINC; COLEUS FORSKOHLII ROOT OIL; CATALASE (MICROCOCCUS LUTEUS); DEXTROSE; ADENOSINE CYCLIC PHOSPHATE; PYRUVIC ACID; ADENOSINE TRIPHOSPHATE; QUATERNIUM-15; METHYLPARABEN; WATER

Active ingredients

Avobenzone 3 %, Homosalate 10%, Octisalate 5 %, and Octocrylene 2.75 %

Purpose

Sunscreen

Uses

- helps prevent sunburn
- if use as directed with other sun protection measures (see Directions), decreases the risk of skin cancer and early skin aging caused by the sun

Warnings

OTHER SAFETY INFORMATION

For external use only

Do not use on damaged or broken skin

When using this product keep out of eyes. Rinse with water to remove. Contents under pressure-do not puncture or incinerate. Do not store at temperatures above 120°F

Stop use and ask a doctor if rash occurs

Keep out of reach of children. If product is swallowed, get medical help or contact a Poison Control Center right away.

OTHER SAFETY INFORMATION

Flammable Do not use near heat, flame or while smoking.

OTHER SAFETY INFORMATION

Use only as directed. Intentional misuse by deliberately concentrating and inhaling the contents can be harmful or fatal.

Directions

- apply liberally and spread evenly by hand 15 minutes before sun exposure
- reapply:
- after 80 minutes of swimming or sweating
- immediately after towel drying
- at least every 2 hours
- Sun Protection Measures. Spending time in the sun increases your risk of skin cancer and early skin aging. To decrease this risk, regularly use a sunscreen with a broad spectrum SPF of 15 or higher and other sun protection measures including:
- limit time in the sun, especially from 10 a.m - 2 p.m.
- wear long-sleeve shirts, pants, hats, and sunglasses
- children under 6 months: Ask a doctor

Inactive Ingredients

Adenosine Cyclic Phesphate, Adenosine Triphosphate, Aloe Barbadensis Leaf Juice, Camelllia Sinensis (Green Tea) Leaf Extract, Ceteareth-20, Cetearyl Alcohol, Coleus Forskohlii Root Extract, Disodium EDTA, EDTA, Fragrance (Parfum), Glucose, Hydrolyzed Soy Protein, Isostearic Acid, Lycium Barbarum (Goji Berry) Fruit Extract, Methylisothiazolinone, Methylparaben, Micrococcus Lysate, Phenoxyethanol, Phenyl Trimethicone, Phospholipids, Plant Amino Acids, Polyperfluoroethoxymethoxy Difluoroethyl PEG Phosphate, Polysorbate 20, Polysorbate 60, Propane, Propylene Glycol, Pyruvic Acid, Quaternium-15, Saccharomyces/Calcium Ferment, Saccharomyces Lysate Extract, Saccharomyces/Magnesium Ferment, Saccharomyces/Zinc Ferment, Sodium Polyacrylate, Stearic Acid, Styrene/Acrylates Copolymer, Tocopheryl Acetate, Triethanolamine, VP/Hexadecene, Water (Aqua)

Other Information

- protect this product from exessive heat and direct sun
- avoid spraying on fabrics - could cause discoloration

Questions or comments?

Call toll free 1-800-SUNCARE

PRINCIPAL DISPLAY PANEL - 170 g Can Label

California Tan

CT

30

Body

Mousse

Sunscreen Mousse

Broad Spectrum SPF 30

Water Resistant

(80 Minutes)

OIL FREE

Net Wt. 6 oz (170g)